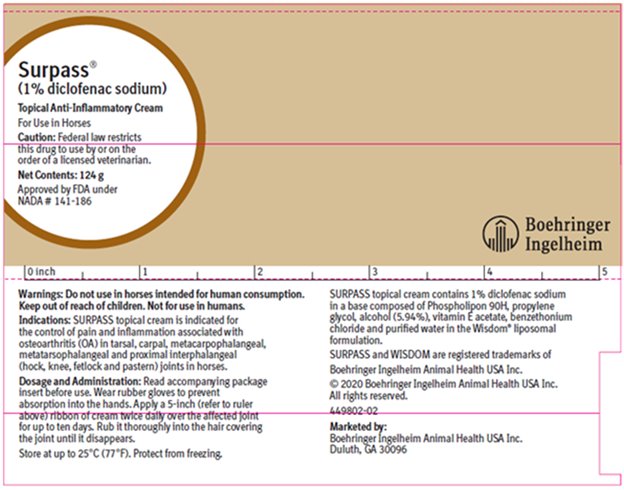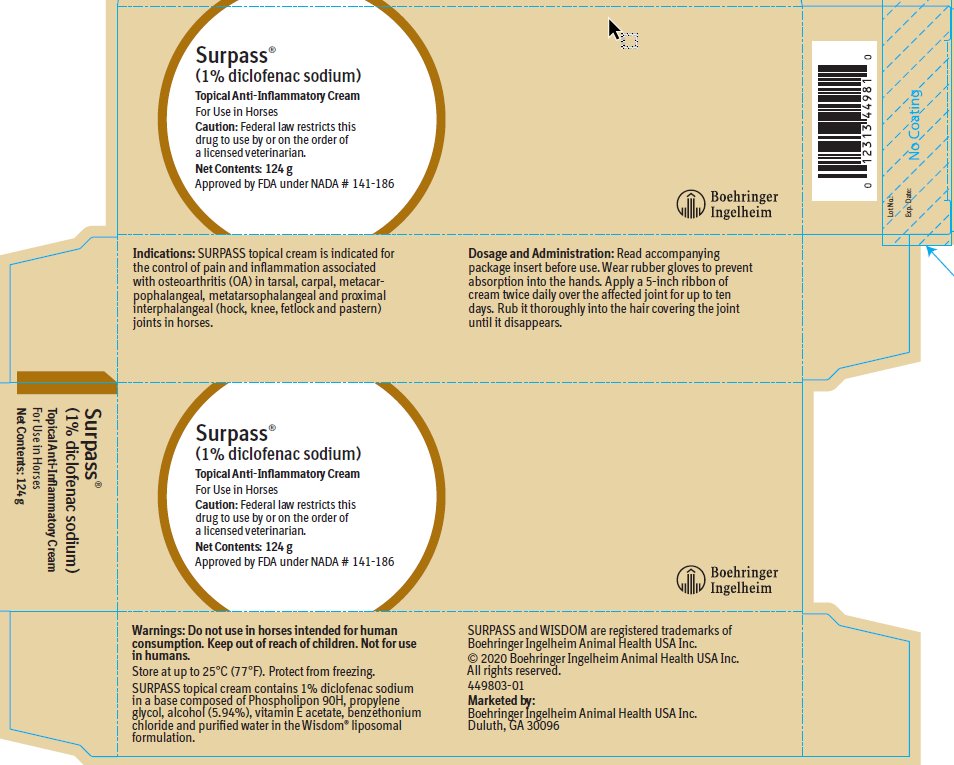 DRUG LABEL: Surpass
NDC: 0010-4498 | Form: CREAM
Manufacturer: Boehringer Ingelheim Animal Health USA Inc.
Category: animal | Type: PRESCRIPTION ANIMAL DRUG LABEL
Date: 20220228

ACTIVE INGREDIENTS: DICLOFENAC SODIUM 0.01 g/1 g
INACTIVE INGREDIENTS: LECITHIN, SOYBEAN 0.10 g/1 g; .ALPHA.-TOCOPHEROL ACETATE, DL- 0.01 g/1 g; PROPYLENE GLYCOL 0.0495 g/1 g; ALCOHOL 0.0594 g/1 g; BENZETHONIUM CHLORIDE 0.0002 g/1 g; WATER 0.77 g/1 g

Surpass®
(1% diclofenac sodium)
Topical Anti-Inflammatory Cream
For Use in Horses

Veterinary Package Insert

Caution:

Federal law restricts this drug to use by or on the order of a licensed veterinarian.

Description:

SURPASS topical cream contains 1% diclofenac sodium. Diclofenac is a non-steroidal anti-inflammatory drug (NSAID) of the phenylacetic acid class. The chemical name for diclofenac is sodium [o- (2,6-dichloroanilino)phenyl] acetate. The empirical formula is C14H10Cl2NNaO2 and the molecular weight is 318.13. SURPASS topical cream contains 1% diclofenac sodium in a base composed of Phospholipon 90H, propylene glycol, alcohol (5.94%), vitamin E acetate, benzethonium chloride and purified water in the Wisdom® liposomal formulation.

Indications:

SURPASS topical cream is indicated for the control of pain and inflammation associated with osteoarthritis (OA) in tarsal, carpal, metacarpophalangeal, metatarsophalangeal and proximal interphalangeal (hock, knee, fetlock and pastern) joints in horses.

Dosage and Administration:

Always provide the Client Information Sheet with the prescription.

Dosage: Apply a five-inch (5") ribbon of SURPASS topical cream twice daily over the affected joint for up to ten days.

Administration: Wear rubber gloves to prevent absorption into the hands. Rub the cream thoroughly into the hair covering the joint until it disappears.

Contraindications:

SURPASS topical cream is contraindicated in animals with known hypersensitivity to diclofenac.

Warnings:

Do not use in horses intended for human consumption.

User Safety: Keep out of reach of children. Not for human use. Consult a physician in case of accidental ingestion by humans.

Wear gloves to prevent absorption into the hands. Direct contact with the skin should be avoided. If contact occurs, the skin should be washed immediately with soap and water.

Animal Safety: For topical use in horses only. Owners should be advised to observe for signs of potential drug toxicity (see Information for Owner or Person Treating Animal and Adverse Reactions).

Precautions:

Exceeding the recommended dosage or treating multiple joints may increase plasma concentrations of diclofenac (see Animal Safety). The systemic effects of excess diclofenac doses that exceed the recommended label amount and duration have not been evaluated.

Horses should undergo a thorough history and physical examination before initiation of NSAID therapy. Appropriate laboratory tests should be conducted to establish hematological and serum biochemical baseline data before and periodically during administration of any NSAID. Owners should be advised to observe for signs of potential drug toxicity (see Information for Owner or Person Treating Animal).

Treatment with SURPASS cream should be terminated if signs such as inappetence, colic, fecal abnormalities, anemia or depression are observed.

As a class, NSAIDs may be associated with gastrointestinal and renal toxicity. When NSAIDs inhibit prostaglandins that cause inflammation, they may also inhibit prostaglandins that maintain normal homeostatic function. These anti-prostaglandin effects may result in clinically significant disease in patients with underlying or preexisting disease more often than in healthy patients. Patients at greatest risk for renal toxicity are those that are dehydrated, on concomitant diuretic therapy, or those with renal, cardiovascular and/or hepatic dysfunction.

Studies to determine the effect of SURPASS topical cream when administered concomitantly with other drugs have not been conducted. Since many NSAIDs possess the potential to induce gastric ulceration, concomitant use of SURPASS cream with any other anti-inflammatory drugs, such as other NSAIDs and corticosteroids, should be avoided. Drug compatibility should be monitored closely in patients receiving adjunctive therapy.

The safety of SURPASS cream has not been investigated in breeding, pregnant or lactating horses, or in horses under one year of age.

Adverse Reactions:

During the field study, one diclofenac-treated horse developed colic on day four of the study and responded to symptomatic treatment. One placebo-treated horse exhibited mildly jaundiced mucous membranes on day five. Adverse reactions during the safety study included a gastric ulcer in one horse that received 5.6X the recommended dosage, diarrhea and uterine discharge in one horse that received 2.8X the recommended dosage, and weight loss in four of the six horses in the 5.6X dosage group.

To report suspected adverse reactions, to obtain a Safety Data Sheet or for technical assistance, call 1-888-637-4251.

For additional information about adverse drug experience reporting for animal drugs, contact FDA at 1-888-FDA-VETS or online at www.fda.gov/reportanimalae.

Information for Owner or Person Treating Animal:

Owners should be advised of the potential for adverse reactions and be informed of the clinical signs associated with NSAID intolerance. Adverse reactions may include: weight loss, colic, diarrhea, or icterus. Serious adverse reactions associated with this drug class can occur without warning and, in rare situations, result in death. Owners should be advised to discontinue NSAID therapy and contact their veterinarian immediately if signs of intolerance are observed. The majority of patients with drug-related adverse reactions recover when the signs are recognized, drug administration is stopped, and veterinary care is initiated.

Clinical Pharmacology:

Diclofenac is a non-steroidal anti-inflammatory drug (NSAID) with analgesic properties. The mechanism of action of diclofenac, like other NSAIDs, is believed to be associated with the inhibition of cyclooxygenase activity.

Effectiveness:

In a controlled field study, 82 horses with osteoarthritis were treated with SURPASS topical cream (42 horses) or placebo (40 horses). Lameness examinations were performed in horses with osteoarthritis associated with the tarsal, carpal, metacarpophalangeal, metatarsophalangeal and proximal interphalangeal joints. Investigators were masked to treatment. Investigators and owners were instructed to apply the test article over the affected joint twice daily (BID) for five days. Actual doses received by individual horses were calculated using tube weight measurements. The mean dose applied during the study was 73 mg per application. Average lameness scores showed statistically significant improvement following treatment with SURPASS topical cream.

One diclofenac-treated horse developed colic and responded to symptomatic treatment on day four of the study. Day five bloodwork for the horse that colicked showed decreases in RBC, Hb and HCT, with an increase in PMNs, compared to pretreatment values. One placebo-treated horse exhibited mildly jaundiced mucous membranes on day five. No other adverse reactions were noted during the study.

Animal Safety:

A controlled safety study was conducted with SURPASS topical cream. Four groups of six healthy adult horses received 0, 0.6, 1.7 or 2.8X the recommended daily dose for twenty-eight days. The daily dose was divided into two applications on day one of the study. For the remainder of the study, the entire daily dose was given at one time on 0, 1, 3 or 5 joints (tarsal, carpal, metacarpophalangeal, metatarsophalangeal, and proximal interphalangeal joints), depending on the dosage group. The control group of six horses was sham-dosed by rubbing the joints daily for twenty-eight days. An additional study group evaluated six horses that received 5.6X the recommended daily dose of SURPASS topical cream distributed over five joints on a single day. This dose group was observed for fourteen days without additional treatment.

Clinical examinations, hematology, serum chemistry, synovial fluid analyses, gross necropsy and histopathology were performed. At necropsy, one horse in the 5.6X group had a glandular gastric ulcer. A horse in the 2.8X group had diarrhea and uterine discharge throughout the study. Four of the six horses in the 5.6X group lost weight during the study.

Dose-dependent increases in diclofenac plasma concentrations were detected in horses in the 1.7X and 2.8X treatment groups.

Storage Information:

Store at up to 25°C (77°F). Protect from freezing.

How Supplied:

SURPASS topical cream is white to pinkish-white and is packaged in 124-gram trilaminate tubes.

Client Information Sheet

Surpass®

(1% diclofenac sodium)

Topical Anti-Inflammatory Cream

For Use in Horses

This summary contains important information about SURPASS topical cream. You should read this information before treating your horse with SURPASS cream. This sheet of information is provided only as a summary and does not take the place of instructions from your veterinarian. Talk to your veterinarian if you have any questions about this information or to learn more about SURPASS topical cream.

1. What is SURPASS topical cream?

SURPASS topical cream contains 1% diclofenac sodium. Diclofenac is a prescription non-narcotic, non-steroidal anti-inflammatory drug (NSAID) that controls pain. Diclofenac is used for the control of pain and inflammation associated with osteoarthritis (OA) in hock, knee, fetlock or pastern joints in horses.

2. What kind of results can I expect when my horse is being treated with SURPASS cream?

Osteoarthritis is a painful condition caused by the progressive deterioration of the cartilage, accompanied by changes in the bone and soft tissues of the joint. This disease is characterized by pain and loss of function of the affected joint.

While SURPASS topical cream is not a cure for osteoarthritis, it does control the pain and inflammation associated with OA and increases the horse’s mobility. The response to SURPASS cream will vary from horse to horse. In most horses, maximum improvement is seen in less than one week.

3. Which horses should not receive treatment with SURPASS topical cream?

SURPASS cream is for topical use in horses only. SURPASS cream should not be used in horses exhibiting allergic reactions to diclofenac. SURPASS topical cream is not for use in horses intended for human consumption. The safety of SURPASS cream has not been determined in horses less than one year of age, in horses used for breeding, pregnant mares, or mares nursing foals.

4. How do I apply SURPASS topical cream to my horse?

Wear gloves to prevent absorption into the hands. Direct contact with the skin should be avoided. If contact occurs, the skin should be washed immediately with soap and water. Apply a five-inch (5") ribbon of SURPASS cream twice daily over the affected joint for up to ten days. Rub it thoroughly into the hair covering the joint until it disappears.

5. What should I tell my veterinarian?

Tell your veterinarian if your horse has experienced allergic reactions to diclofenac or other medications. Tell your veterinarian if your horse is pregnant or nursing a foal, or if you intend to breed the horse. Tell your veterinarian if your horse has ever been diagnosed with an ulcer.

6. What possible side effects may occur in my horse’s therapy?

Horses should undergo a thorough history and physical examination by a veterinarian before the initiation of any SURPASS therapy. Using more than the recommended amount of SURPASS topical cream (for example, by treating multiple joints) has not been tested and is not recommended. Excessive doses to the skin have been shown to enter the bloodstream and this may increase the risk of side effects. Adverse reactions associated with NSAIDs may include: weight loss, colic, diarrhea, or yellowing of the gums, skin, or whites of the eyes (jaundice). Serious adverse reactions associated with this drug class can occur without warning and, in rare situations, result in death. Discontinue the use of SURPASS cream and contact your veterinarian immediately if these signs are observed. The majority of patients with drug-related adverse reactions recover when the signs are recognized, drug administration is stopped, and veterinary care, if appropriate, is initiated.

7. What precautions should I take before administering SURPASS topical cream?

Wear gloves to prevent absorption into the hands. Direct contact with the skin should be avoided. If contact occurs, the skin should be washed immediately with soap and water.

SURPASS topical cream should only be applied to horses. Keep SURPASS cream and all medications out of the reach of children. SURPASS cream is not for human use. Contact a physician in case of accidental ingestion by people.

8. Can SURPASS topical cream be given with other medications?

SURPASS cream should not be given with any other anti-inflammatory drugs, such as other NSAIDs (for example, aspirin, phenylbutazone, flunixin) and corticosteroids (for example, cortisone, prednisone, dexamethasone, triamcinolone). Tell your veterinarian about all medicines that you are planning to administer in addition to SURPASS cream. These should include other medications that you can obtain without a prescription.

9. How should I store SURPASS topical cream?

Store at up to 25°C (77°F). Protect from freezing. Keep SURPASS cream and all medications out of reach of children.

10. What else should I know about SURPASS topical cream?

This document provides a summary of information about SURPASS topical cream. If you have questions or concerns about SURPASS cream or osteoarthritis pain, talk to your veterinarian.

As with all prescription medications, SURPASS cream should only be administered to the patient for whom it was prescribed, and should only be used as prescribed.

To report a suspected adverse reaction, call 1-888-637-4251.

SURPASS is a registered trademark of Boehringer Ingelheim Animal Health USA Inc.

Marketed by:
Boehringer Ingelheim Animal Health USA Inc.
Duluth, GA 30096

© 2020 Boehringer Ingelheim Animal Health USA Inc. All rights reserved.

449804-01

Principal Display Panel – Tube, 124 g

Surpass®

(1% diclofenac sodium)

Topical Anti-Inflammatory Cream

For Use in Horses

Caution: Federal law restricts this drug to use by or on the order of a licensed veterinarian.

Net Contents: 124 g

Approved by FDA under NADA # 141-186

Principal Display Panel – Display Carton, 124 g

Surpass®

(1% diclofenac sodium)

Topical Anti-Inflammatory Cream

For Use in Horses

Caution: Federal law restricts this drug to use by or on the order of a licensed veterinarian.

Net Contents: 124 g

Approved by FDA under NADA # 141-186